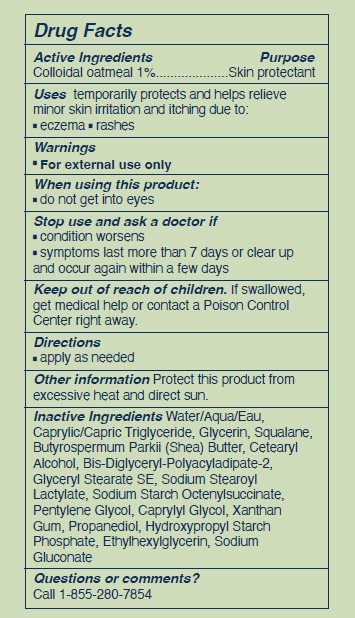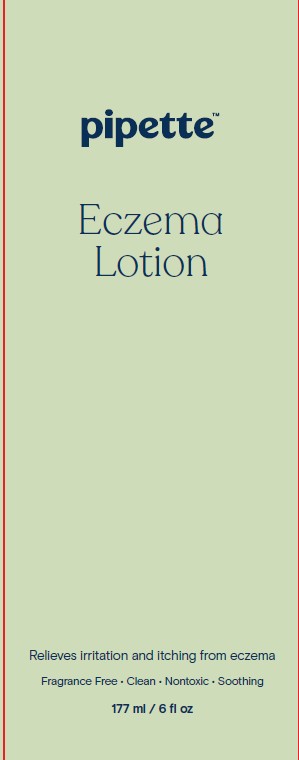 DRUG LABEL: Pipette Eczema
NDC: 84723-004 | Form: LOTION
Manufacturer: Pipette LLC
Category: otc | Type: HUMAN OTC DRUG LABEL
Date: 20250709

ACTIVE INGREDIENTS: OATMEAL 10 mg/1 mL
INACTIVE INGREDIENTS: SODIUM GLUCONATE; WATER; CAPRYLIC/CAPRIC TRIGLYCERIDE; CETEARYL ALCOHOL; GLYCERIN; SQUALANE; BUTYROSPERMUM PARKII (SHEA) BUTTER; BIS-DIGLYCERYL POLYACYLADIPATE-2; GLYCERYL STEARATE SE; SODIUM STEAROYL LACTYLATE; PENTYLENE GLYCOL; CAPRYLYL GLYCOL; XANTHAN GUM; PROPANEDIOL; ETHYLHEXYLGLYCERIN

Pipette Eczema Lotion

Active Ingredients

Colloidal Oatmeal 1 %

Purpose

Skin protectant

Uses

Temporarily protects and helps relieve minor skin irritation and itching due to:

• eczema • rashes

Warnings

- For external use only

When using this product:

- do not get into eyes

Stop use and ask a doctor if

- condition worsens
- symptoms last more than 7 days or clear up and occur again within a few days

Keep out of reach of children.

- If swallowed, get medical help or contact a Poison Control Center right away.

Directions

- apply as needed

Other Information

Protect this product from excessive heat and direct sun.

Inactive Ingredients

Water/Aqua/Eau, Caprylic/Capric Triglyceride, Glycerin, Squalane, Butyrospermum Parkii (Shea) Butter, Cetearyl Alcohol, Bis Diglyceryl-Polyacyladipate-2, Glyceryl Stearate SE, Sodium Stearoyl Lactylate, Sodium Starch Octenylsuccinate, Pentylene Glycol, Caprylyl Glycol, Xanthan Gum, Propanediol, Hydroxypropyl Starch Phosphate, Ethylhexylglycerin, Sodium Gluconate

Questions or comments?

Call 1-855-280-7854